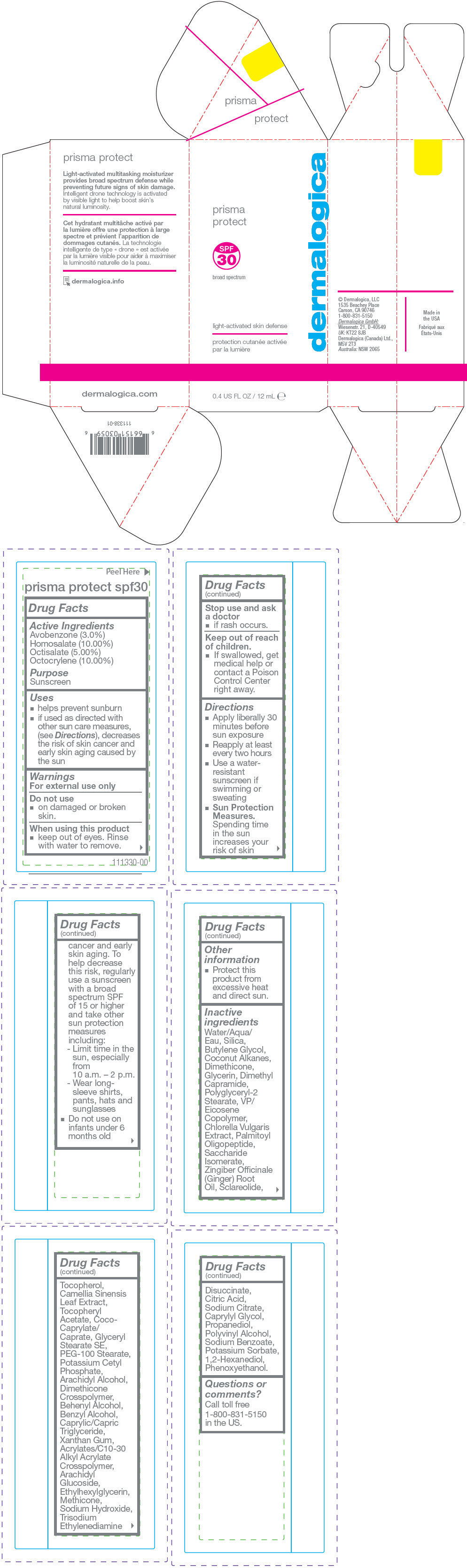 DRUG LABEL: Prisma Protect SPF 30
NDC: 68479-805 | Form: LOTION
Manufacturer: Dermalogica, Inc.
Category: otc | Type: HUMAN OTC DRUG LABEL
Date: 20190307

ACTIVE INGREDIENTS: Avobenzone 30 mg/1 mL; Homosalate 100 mg/1 mL; Octisalate 50 mg/1 mL; Octocrylene 100 mg/1 mL
INACTIVE INGREDIENTS: Water; Butylene Glycol; Silicon Dioxide; Coconut Alkanes; Dimethicone; Glycerin; Dimethyl Capramide; Polyglyceryl-2 Stearate; Vinylpyrrolidone/Eicosene Copolymer; Chlorella Vulgaris; Grapefruit Oil; Saccharide Isomerate; Ginger Oil; Sclareolide; Tocopherol; Green Tea Leaf; .Alpha.-Tocopherol Acetate; Coco-Caprylate/Caprate; Glyceryl Stearate SE; PEG-100 Stearate; Potassium Cetyl Phosphate; Arachidyl Alcohol; Dimethicone Crosspolymer (450000 MPA.S at 12% in Cyclopentasiloxane); Docosanol; Benzyl Alcohol; Medium-chain Triglycerides; Xanthan Gum; Ethyl Acrylate/Methacrylic Acid/Steareth-20 Methacrylate Copolymer; Arachidyl Glucoside; Ethylhexylglycerin; Methicone (20 CST); Sodium Hydroxide; Trisodium Ethylenediamine Disuccinate; Citric Acid Monohydrate; Sodium Citrate, Unspecified Form; Caprylyl Glycol; Propanediol; Polyvinyl Alcohol, Unspecified; Sodium Benzoate; Potassium Sorbate; 1,2-Hexanediol; Phenoxyethanol

Prisma Protect SPF 30

Drug Facts

Active Ingredients

Avobenzone (3.0%)
Homosalate (10.00%)
Octisalate (5.00%)
Octocrylene (10.00%)

Purpose

Sunscreen

Uses

- helps prevent sunburn
- if used as directed with other sun care measures, (see Directions), decreases the risk of skin cancer and early skin aging caused by the sun

Warnings

For external use only

Do not use

- on damaged or broken skin.

When using this product

- keep out of eyes. Rinse with water to remove.

Stop use and ask a doctor

- if rash occurs.

Keep out of reach of children.

- If swallowed, get medical help or contact a Poison Control Center right away.

Directions

- Apply liberally 30 minutes before sun exposure
- Reapply at least every two hours
- Use a water-resistant sunscreen if swimming or sweating
- Sun Protection Measures. Spending time in the sun increases your risk of skin cancer and early skin aging. To help decrease this risk, regularly use a sunscreen with a broad spectrum SPF of 15 or higher and take other sun protection measures including:
  - Limit time in the sun, especially from 10 a.m. – 2 p.m.
  - Wear long-sleeve shirts, pants, hats and sunglasses
- Do not use on infants under 6 months old

Other information

- Protect this product from excessive heat and direct sun.

Inactive ingredients

Water/Aqua/Eau, Silica, Butylene Glycol, Coconut Alkanes, Dimethicone, Glycerin, Dimethyl Capramide, Polyglyceryl-2 Stearate, VP/Eicosene Copolymer, Chlorella Vulgaris Extract, Palmitoyl Oligopeptide, Saccharide Isomerate, Zingiber Officinale (Ginger) Root Oil, Sclareolide, Tocopherol, Camellia Sinensis Leaf Extract, Tocopheryl Acetate, Coco-Caprylate/Caprate, Glyceryl Stearate SE, PEG-100 Stearate, Potassium Cetyl Phosphate, Arachidyl Alcohol, Dimethicone Crosspolymer, Behenyl Alcohol, Benzyl Alcohol, Caprylic/Capric Triglyceride, Xanthan Gum, Acrylates/C10-30 Alkyl Acrylate Crosspolymer, Arachidyl Glucoside, Ethylhexylglycerin, Methicone, Sodium Hydroxide, Trisodium Ethylenediamine Disuccinate, Citric Acid, Sodium Citrate, Caprylyl Glycol, Propanediol, Polyvinyl Alcohol, Sodium Benzoate, Potassium Sorbate, 1,2-Hexanediol, Phenoxyethanol.

Questions or comments?

Call toll free 1-800-831-5150 in the US.

PRINCIPAL DISPLAY PANEL - 12 mL Tube Carton

prisma
protect

SPF
30
broad spectrum

dermalogica

light-activated skin defense

0.4 US FL OZ / 12 mL ℮